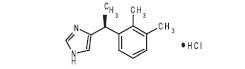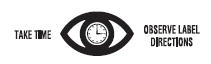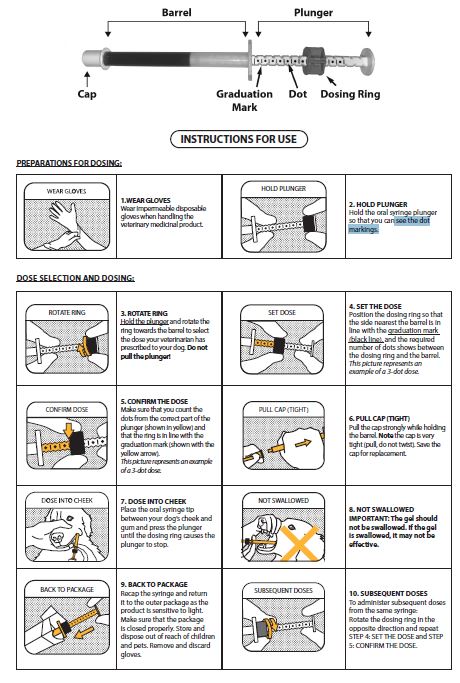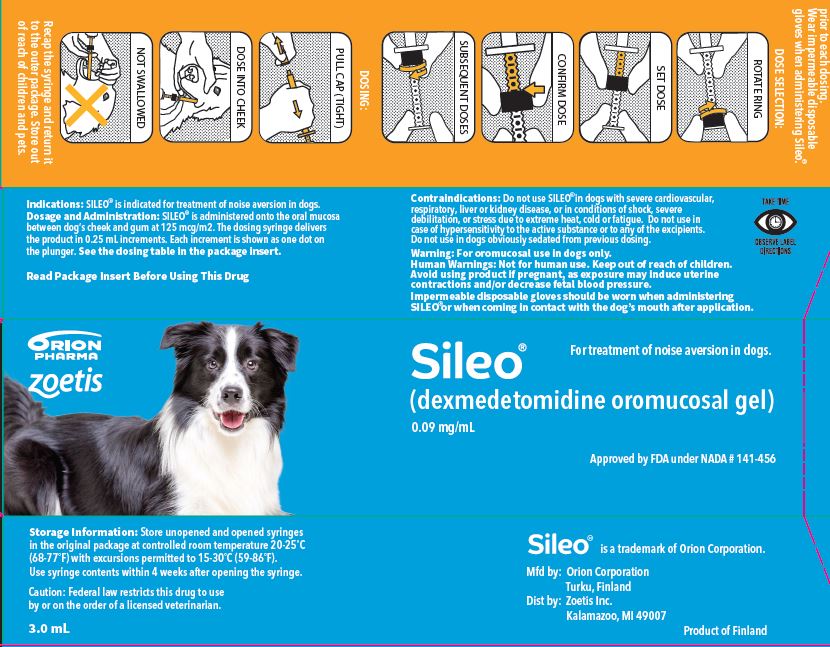 DRUG LABEL: Sileo
NDC: 54771-1050 | Form: GEL
Manufacturer: Zoetis Inc.
Category: animal | Type: PRESCRIPTION ANIMAL DRUG LABEL
Date: 20240718

ACTIVE INGREDIENTS: DEXMEDETOMIDINE 0.09 mg/1 mL

SILEO®

Approved by FDA under NADA # 141-456
Sileo®
(dexmedetomidine oromucosal gel)
Each mL of SILEO contains 0.09 mg dexmedetomidine (equivalent to 0.1 mg dexmedetomidine hydrochloride).
For oromucosal use in dogs only. Not intended for ingestion.

CAUTION

Federal law (USA) restricts this drug to use by or on the order of a licensed veterinarian

DESCRIPTION

SILEO (dexmedetomidine oromucosal gel) is a synthetic alpha-2 adrenoceptor agonist. Each ml of SILEO contains 0.09 mg dexmedetomidine (equivalent to 0.1 mg dexmedetomidine hydrochloride). The chemical name is (+)-4-[1-(2,3-dimethylphenyl) ethyl]-1H-imidazole monohydrochloride. It is a white, or almost white, crystalline, water soluble substance having a molecular weight of 236.7. The molecular formula is C13 H16 N2 HCl and the structural formula is:

Structure

INDICATIONS

SILEO is indicated for the treatment of noise aversion in dogs.

DOSAGE AND ADMINISTRATION

Always provide the Client Information Sheet with SILEO and instruct the client how to properly operate the SILEO dosing syringe (see Client Information Sheet for Owner/Handler Use and Safety).
SILEO is administered onto the oral mucosa between the dog’s cheek and gum at the dose of 125 mcg/m2. The gel is absorbed through the oral mucosa and therefore it should NOT be swallowed. If the gel is swallowed, the product may not be effective. If the gel is swallowed, do not repeat the dose for at least two hours.
The following table provides the acceptable dosage for each weight range. Each dot (●) represents 0.25 mL of SILEO.
Each ml contains the equivalent to 0.1mg dexmedetomidine hydrochloride.

Table 1. Dosage by body weight

Bodyweight (lb) | Number of dots
4.4-12.1 | 1 ●
12.2-26.5 | 2 ●●
26.6-44.0 | 3 ●●●
44.1-63.9 | 4 ●●●●
64.0-86.0 | 5 ●●●●●
86.1-110.2 | 6 ●●●●●●
110.3-137.8 | 7 ●●●●●●●
137.9-166.4 | 8 ●●●●●●●●
166.5-196.2 | 9 ●●●●●●●●●
196.3-220.5 | 10 ●●●●●●●●●●

If the dose is more than 6 dots, divide the dose between both sides of the mouth.

The first dose of SILEO should be administered approximately
30-60 minutes before the fear and/or anxiety-eliciting noise stimulus, immediately after the dog shows first signs of anxiety or fear related to noise, or when the owner detects a typical noise stimulus (e.g. sound of fireworks) eliciting anxiety or fear in the dog. Typical signs of anxiety and fear associated with noise aversion are panting, trembling, pacing, seeking people, trying to hide, trying to escape, freezing behavior, refusing to eat food or treats, inappropriate urination or defecation, and salivation.
Administering SILEO without use of the SILEO syringe will result in incorrect dosing, which may result in lack of efficacy or overdose.
Dosing should be performed by an adult. Impermeable disposable gloves should be worn when administering SILEO and when handling the SILEO syringe.
If noise lasts longer than 2-3 hours and the dog’s signs of fear and/or anxiety reappear, another dose may need to be given. To avoid overdosing, there should always be at least two hours’ pause between dosages. No more than 5 doses can be given during one noise event.
A partially used syringe can be used again within 2 weeks after initial opening, if there is enough gel for a complete dose for the dog. To minimize the risk of incorrect dosing, a partially used syringe that does not have enough gel for a complete dose should not be used.
Any unused product or waste material should be disposed of according

CONTRAINDICATIONS

Do not use SILEO in dogs with severe cardiovascular, respiratory, liver or kidney disease, or in conditions of shock, severe debilitation, or stress due to extreme heat, cold or fatigue. Do not use in dogs with hypersensitivity to dexmedetomidine or to any of the excipients.

WARNINGS

Human Safety: Not for human use. Keep out of reach of children.

Avoid administering the product if pregnant, as exposure may induce uterine contractions and/or decrease fetal blood pressure.

Appropriate precautions should be taken while handling and using filled syringes. Impermeable disposable gloves should be worn when handling the syringe, administering SILEO, or when coming in contact with the dog’s mouth after application.

If skin is damaged, dexmedetomidine can be absorbed into the body. In case of skin contact, wash with soap and water. Remove contaminated clothing.

SILEO can be absorbed following direct exposure to skin, eyes, or mouth. In case of accidental eye exposure, flush with water for 15 minutes. If wearing contact lenses, eyes should be rinsed first, then remove contact lenses and continue rinsing, then seek medical advice immediately.

Accidental exposure may cause sedation and changes in blood pressure. In case of accidental exposure, seek medical attention immediately. Exposure to the product may induce a local or systemic allergic reaction in sensitized individuals.

Note to physician: This product contains an alpha-2 adrenoceptor agonist.

The safety data sheet (SDS) contains more detailed occupational safety information. To report adverse reactions in users or to obtain a copy of the SDS for this product call 1-888-963-8471.

Animal Safety: SILEO should not be administered in the presence of pre-existing hypotension, hypoxia, or bradycardia. Sensitive dogs may experience a drop in body temperature and heart rate, and may appear sedated. These dogs should be kept warm and not offered food or water until SILEO’s effects have worn off (usually within a few hours). Do not use in dogs sedated from previous dosing.

PRECAUTIONS

SILEO is not meant to be swallowed. Instead, it must be placed onto the mucosa between the dog’s cheek and gum. If SILEO is swallowed, the product may not be effective. If SILEO is swallowed, do not repeat the dose for at least two hours. Feeding and giving treats within 15 minutes after administration should be avoided.
The use of other central nervous system depressants may potentiate the effects of SILEO.
As with all alpha-2 adrenoceptor agonists, the potential for isolated cases of hypersensitivity, including paradoxical response (excitation), exists.
SILEO has not been evaluated in dogs younger than 16 weeks of age or in dogs with dental or gingival diseases that could have an effect on SILEO’s absorption. SILEO has not been evaluated for aversion behaviors to thunderstorms.
The safety and effectiveness of SILEO in breeding, pregnant, and lactating dogs has not been evaluated. Administration to pregnant dogs may induce uterine contractions and/or decrease fetal blood pressure.

ADVERSE REACTIONS

In a well-controlled European field study, which included a total of 182 dogs ranging from 2 to 17 years of age and representing both mixed and pure breed dogs (89 treated with dexmedetomidine oromucosal gel and 93 treated with control), no serious adverse reactions were attributed to administration of dexmedetomidine oromucosal gel.

Table 2 shows the number of dogs displaying adverse reactions (some dogs experienced more than one adverse reaction).

Table 2. Adverse Reactions - Number (%) of dogs

Adverse Reaction | Control; N = 93 | Dexmedetomidine 125 mcg/m2; N = 89
Emesis | 1 (1.1) | 4 (4.5)
Gastroenteritis | 0 | 1 (1.1)
Periorbital edema | 0 | 1 (1.1)
Drowsiness | 0 | 1 (1.1)
Sedation | 0 | 1 (1.1)

Pale mucous membranes were frequently seen in dogs treated with dexmedetomidine oromucosal gel. In most cases, the effect was transient and no adverse reactions due to mucosal irritation were reported.

In a second well-controlled European field study which included a total of 36 dogs ranging from 2 to 17 years of age and representing both mixed and pure breed dogs (12 treated with dexmedetomidine oromucosal gel at 125 mcg/m2, 12 treated with dexmedetomidine oromucosal gel at 250 mcg/m2, and 12 treated with a vehicle control), no serious adverse reactions were attributed to administration of dexmedetomidine oromucosal gel.Table 3 shows the number of dogs displaying adverse reactions (some dogs experienced more than one adverse reaction).

Table 3. Adverse Reactions - Number (%) of dogs

Adverse; Reaction | Control; N = 12 | Dexmedetomidine 125 mcg/m2; N = 12 | Dexmedetomidine 250 mcg/m2; N = 12
Sedation | 0 | 2 (16.7) | 4 (33.3)
Lack of; effectiveness | 4 (33.3) | 0 | 1 (8.3)
Urinary; incontinence | 0 | 1 (8.3) | 1 (8.3)
Emesis | 0 | 2 (16.7) | 0
Head tremor | 0 | 0 | 1 (8.3)
Inappropriate; urination | 0 | 1 (8.3) | 0
Ataxia | 0 | 0 | 1 (8.3)
Mydriasis | 0 | 0 | 1 (8.3)
Anxiety; disorder | 0 | 0 | 1 (8.3)
Tachypnea | 1 (8.3) | 0 | 0
Lethargy | 1 (8.3) | 0 | 0
Tachycardia | 1 (8.3) | 0 | 0

CONTACT INFORMATION

For a copy of the Safety Data Sheet or to report adverse reactions, call Zoetis Inc. at 1-888-963-8471. For additional information about adverse drug experience reporting for animal drugs, contact FDA at 1-888-FDA-VETS or www.fda.gov/reportanimalae.

CLINICAL PHARMACOLOGY

Dexmedetomidine is a potent and selective alpha-2 adrenoceptor agonist that inhibits the release of noradrenaline from noradrenergic neurons. A reduction of heart rate may occur. In a clinical safety study the mean heart rate dropped from 127 bpm to 98 bpm for dogs treated with the dexmedetomidine gel.
Oral bioavailability of dexmedetomidine is poor due to extensive first-pass metabolism. No measurable concentrations were found after gastro-intestinal tubing of dexmedetomidine to dogs. When administered via the oral mucosa, enhanced bioavailability is observed as a result of absorption in the oral cavity and the avoidance of first-pass metabolism in the liver.
The maximum concentration of dexmedetomidine occurs at about 0.6 hours after both IM and oromucosal administration in dogs. In a pharmacokinetic study in dogs, the oromucosal mean bioavailability of dexmedetomidine was 28%. The apparent volume of distribution of the drug is 0.9 L/kg. In the canine circulation, dexmedetomidine is largely bound to plasma proteins (93%).
Dexmedetomidine is eliminated by biotransformation mainly in the liver with a half-life ranging from 0.5 to 0.7 hours after intravenous (IV) administration and 0.5 to 3 hours after oromucosal administration in dogs. Metabolism accounts for more than 98% of the elimination. Known metabolites show no or negligible activity. Metabolites are excreted mainly in the urine with a minor fraction found in the feces.

ANIMAL SAFETY

Canine safety study with dexmedetomidine hydrochloride injectable

In a laboratory study of dexmedetomidine hydrochloride injection, doses of 375, 1125 and 1875 mcg/m2 were administered once daily IV or doses of 500, 1500 and 2500 mcg/m2 [low, mid, and high doses, respectively] were administered once daily IM on three consecutive days.
Dexmedetomidine-induced sedation occurred on each dosing day at all dose levels from 2 to 8 hours post-dosing. The duration of sedation increased with the dosage level. A decreased respiratory rate was observed in all groups on each day, but returned to normal within 4 hours in the low IV and IM groups and within
8 hours in the mid and high IV and IM groups. A decreased rectal temperature was observed in all groups on each day. In the low IV and IM groups, the rectal temperature returned to normal or near normal within
4 hours and in the mid and high IV and IM groups within 8 hours. A decreased heart rate was observed in all groups on each day, with greater decreases in the IV dosing groups. In the low groups, the duration of decrease was 2 hours with the values returning to normal 4 hours after dosing. In the mid groups, the duration of decrease was 4 hours with the values returning to normal 8 hours after dosing. In the high IV dose group, the values also returned to normal at 8 hours after dosing. However, in the high IM group, the values were still slightly depressed at 8 hours after dosing; the values returned to normal by 24 hours after dosing. On electrocardiography, QT time was prolonged in all groups due to decreased heart rate. In the low and mid IM groups, one case each of second degree A-V-block was observed. In the high IM group, one dog had first and second degree A-V block.
In the mid IV group, two dogs had second degree A-V block and one dog had first and second degree A-V block. In the mid and high IM groups, one dog each had elevated alanine aminotransferase (ALT) values. In the high IV group, two dogs had elevated ALT values.
Dexmedetomidine was well tolerated in the study even at the high doses, and adverse effects on physiology were related to the pharmacology of the drug. There were no toxicological effects on body weight, clinical variables, gross or microscopic pathology.

EFFECTIVENESS

SILEO was evaluated in a European randomized multi-center, double-blind, vehicle-controlled field study. Effectiveness was evaluated in client-owned dogs, ranging in age between 2 and 17 years, and in body weight between 4 and 67 kg. A total of 187 dogs were randomized, 144 of which were evaluated for effectiveness: 71 dogs received 125 mcg/m2 of dexmedetomidine oromucosal and 73 dogs received the vehicle control gel up to 5 times as needed with a minimum interval of 2 hours between doses. All dogs had in previous years suffered from acute fear and/or anxiety due to fireworks.
The first dose was given on New Year’s Eve before or as soon as the dog showed the first signs of becoming anxious and/or fearful due to fireworks. Re-dosing could be performed as soon as the dog again demonstrated noise aversion behaviors, but at least 2 hours after the previous dose to allow time to assess observable effects of treatment and to avoid potential cumulative effects of dexmedetomidine.
For the first co-primary endpoint, the proportion of dogs with owner-assessed good or excellent treatment effect was higher in dogs treated with dexmedetomidine oromucosal gel (53/71 dogs) than in those administered control (24/73 dogs). The proportion of dogs with some, no, or worse effect was higher in dogs administered control (49/73 dogs) than in those treated with dexmedetomidine (18/71 dogs). Refer to Table 4. below.

Table 4. Owner assessment of treatment effect/score by treatment group

Treatment; Effect | Dexmedetomidine | Control | Total
 | N=71 | N=73 | N=144
 | n(%) | n(%) | n(%)
1 Excellent effect | 12 (16.9) | 8 (11) | 20 (13.9)
2 Good effect | 41 (57.7) | 16 (21.9) | 57 (39.6)
3 Some effect | 7 (9.9) | 14 (19.1) | 21 (14.6)
4 No effect | 8 (11.2) | 32 (43.8) | 40 (27.7)
5 Worse | 3 (4.2) | 3 (4) | 6 (4.2)

There was a statistically significant difference (p<0.0001) between dexmedetomidine and control in favor of dexmedetomidine. The odds ratio was 5.5876, with 95% confidence interval (2.7635, 11.2976).
For the second co-primary variable, the mean sum of behavior scores over the treatment period was significantly different between dexmedetomidine and control (p=0.0069). Behavior scores consisted of a cumulative score using a number of outward signs of noise aversion in dogs such as panting, trembling, vocalizing, and seeking people. The mean score was lower (better) for the dexmedetomidine oromucosal gel treated group than for the control group (LSMeans: 4.9661, 7.2456 respectively). Refer to Table 5 below.

Table 5. Mean behavioral sum scores by treatment and time point

Dosing Time Point | Dexmedetomidine | Control
Dosing Time Point | Sum of Behavior Scores; (mean/number of animals)
Screening | 18.75/71 | 19.01/73
Prior to dose 1 | 5.04/71 | 4.96/73
1 hour post-dose 1 | 3.75/68 | 4.72/71
Prior to dose 2 | 7.93/68 | 9.11/70
1 hour post-dose 2 | 4.21/52 | 9.1/60
Prior to dose 3 | 8.26/38 | 17.5/44
1 hour post-dose 3 | 6.35/34 | 11.0/39
Prior to dose 4 | 6.92/12 | 12.95/21
1 hour post-dose 4 | 5.42/12 | 12.7/21

Of the different types of behaviors, dogs treated with dexmedetomidine oromucosal gel displayed less panting, trembling and trying to hide than those treated with the control gel.

HOW SUPPLIED

SILEO is packaged in HDPE dosing syringe enabling doses from 0.25 to 3 ml. The syringe is fitted with plunger, dosing ring and end cap. Each syringe is further packed into a carton with a label and a leaflet.
Package sizes: (1 syringe per carton) 1 x 3 ml, 3 x 3 ml, 5 x 3 ml, 10 x 3 ml, 20 x 3 ml.
Not all package sizes may be marketed.

STORAGE INFORMATION

Store unopened and opened syringes in the original package at controlled room temperature 20-25°C (68-77°F) with excursions permitted to 15-30°C (59-86°F). Use syringe contents within 4 weeks after opening the syringe.

SILEO® is a trademark of Orion Corporation.

Mfd by:
Orion Pharma
Orion Corporation
Turku, Finland
Dist by:
Zoetis Inc.
Kalamazoo, MI 49007
Revised: June 2023
159395-1

INSTRUCTIONS FOR USE

KEEP THIS CLIENT INFORMATION SHEET IN THE CARTON WITH THE SILEO DOSING SYRINGE
REVIEW PRIOR TO GIVING EACH DOSE TO YOUR DOG

SILEO (dexmedetomidine oromucosal gel)

CLIENT INFORMATION SHEET FOR OWNER/HANDLER USE AND SAFETY

This sheet summarizes the basic information about SILEO and does not replace the instructions from your veterinarian. Talk to your veterinarian if you have questions regarding any part of this information or if you want to know more about SILEO. The syringe must be used in order to correctly dose the drug to your dog. You may use either a full, unused syringe or a partially used syringe that contains enough gel for the desired dose.

What is SILEO?

SILEO is a prescription product containing dexmedetomidine hydrochloride. It is used to treat noise aversion in dogs. Typical signs of anxiety and fear associated with noise aversion are panting, trembling , pacing, seeking people, trying to hide, trying to escape, freezing behavior, refusing to eat food or treats, inappropriate urination and/or defecation, and salivation. SILEO is packaged in a syringe that can be used to apply more than one dose. The medication should not be swallowed by your dog but should be placed in the dog’s mouth between the cheek and gum, so that it can be absorbed into the bloodstream. If SILEO is swallowed, it may not be effective. If you think this has happened, you should wait for two hours and if your dog is showing signs of fear and/or anxiety, then administer another dose.

How should the product be handled?

You should wear impermeable disposable gloves when administering the product and when handling the dosing syringe. Avoid administering the product if pregnant, as exposure may induce uterine contractions and/or decrease fetal blood pressure.

When to administer and what should I expect after administering SILEO?

The first dose of SILEO should be given immediately after your dog shows first signs of fear and/or anxiety associated with noise, or when the typical noise stimulus (e.g. sound of fireworks) inducing anxiety and/or fear in your dog is detected. If the dose for your dog is more than 6 dots, divide the dose between both sides of the mouth. The drug takes effect after approximately 30 minutes to one hour. Your dog should show less intense noise aversion behavior, despite the ongoing noise. Some dogs might be more sensitive to the drug; if your dog appears drowsy, keep it warm and do not offer food or water until the effect of the drug has worn off. This will normally happen within a few hours.

What should I do if SILEO does not work?

If you think that SILEO is not working, do not re-dose and contact your veterinarian to discuss further treatment options.

If needed, is it possible to give another dose of SILEO?

If noise lasts longer than 2-3 hours and your dog is still showing signs of fear and/or anxiety or the signs of fear and anxiety reappear, you may need to give your dog another dose. To avoid overdosing, there should always be at least two hours’ pause between dosages. Dogs sedated from previous dosing should not be given SILEO. No more than 5 doses can be given during one noise event. You can use a partially used syringe again within 48 hours after initial opening, if there is enough gel for a complete dose for your dog. To minimize the risk of incorrect dosing, do not use a partially used syringe that does not have enough gel for a complete dose. Any unused product or waste material should be disposed of according to local law and Federal prescription drug disposal guidelines. Ask your veterinarian for this information.

What should I do if I have accidently given my dog too much SILEO?

Contact your veterinarian immediately.

What if I get the gel in my eyes, nose, or mouth?

The drug can be absorbed into your body through your eyes, nose, or mouth. If it comes in contact with your eyes, nose, or mouth, flush with water for 15 minutes. If wearing contact lenses, eyes should be rinsed first, then remove contact lenses and continue rinsing, then seek medical advice immediately. If the drug is absorbed into your body, it can cause symptoms such as lowered blood pressure (which may result in dizziness; fainting; lack of concentration; blurred vision; nausea; cold, clammy, or pale skin; rapid, shallow breathing), sleepiness, and slower heart rate. Share the package information with your physician and tell the physician that the product contains an alpha-2 adrenoceptor agonist.

What if I get the gel on my skin?

You should wear impermeable disposable gloves when administering this product. If you have cuts or chapped skin, the drug can be absorbed into your body. In case of skin contact, wash immediately with large amounts of water. Remove contaminated clothing. Contact your physician if you have any questions or concerns. To report adverse reactions, call: 1-888-963-8471.

What else should I know about SILEO?

As with all prescription medicine, SILEO should only be given to the dog for which it was prescribed. This sheet provides a summary of information about SILEO. If you have any questions or concerns about SILEO or its effects on your dog, talk to your veterinarian or health care provider.

Which dogs should not take SILEO?

Dogs with severe cardiovascular, respiratory, liver or kidney disease or in dogs sedated from previous dosing should not be given SILEO.

What are the possible side effects that may occur in my dog after being given SILEO?

Possible side effects include vomiting, diarrhea, sedation, decreased heart rate, decreased respiratory rate and pale gums.

How do I store SILEO?

Store unopened and opened syringes at room temperature in the original package, as SILEO is sensitive to light. If syringe contents are not used within 4 weeks after opening the syringe, the syringe should be discarded. Store out of reach of children and pets.

PRINCIPAL DISPLAY PANEL - Carton

159414-2